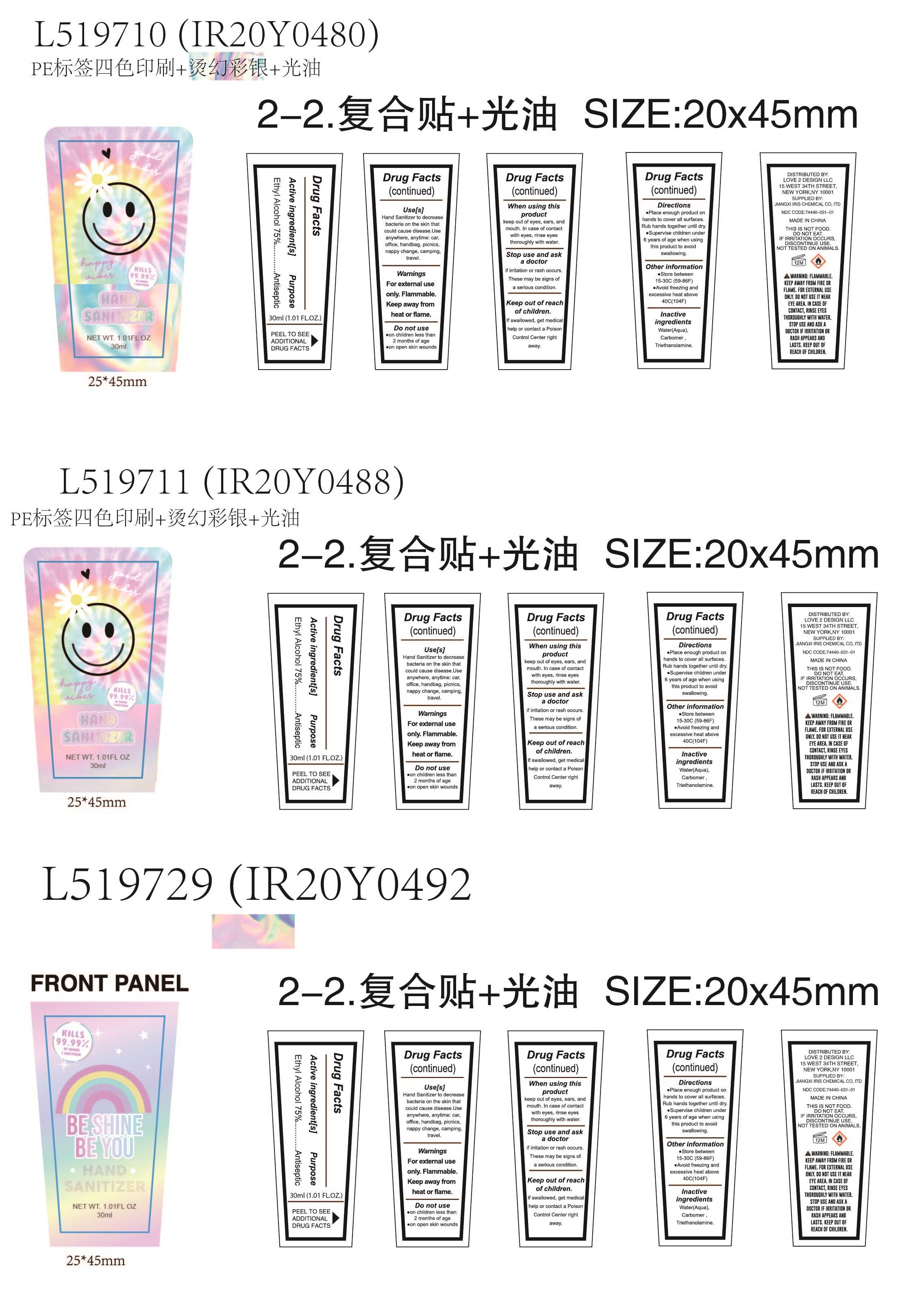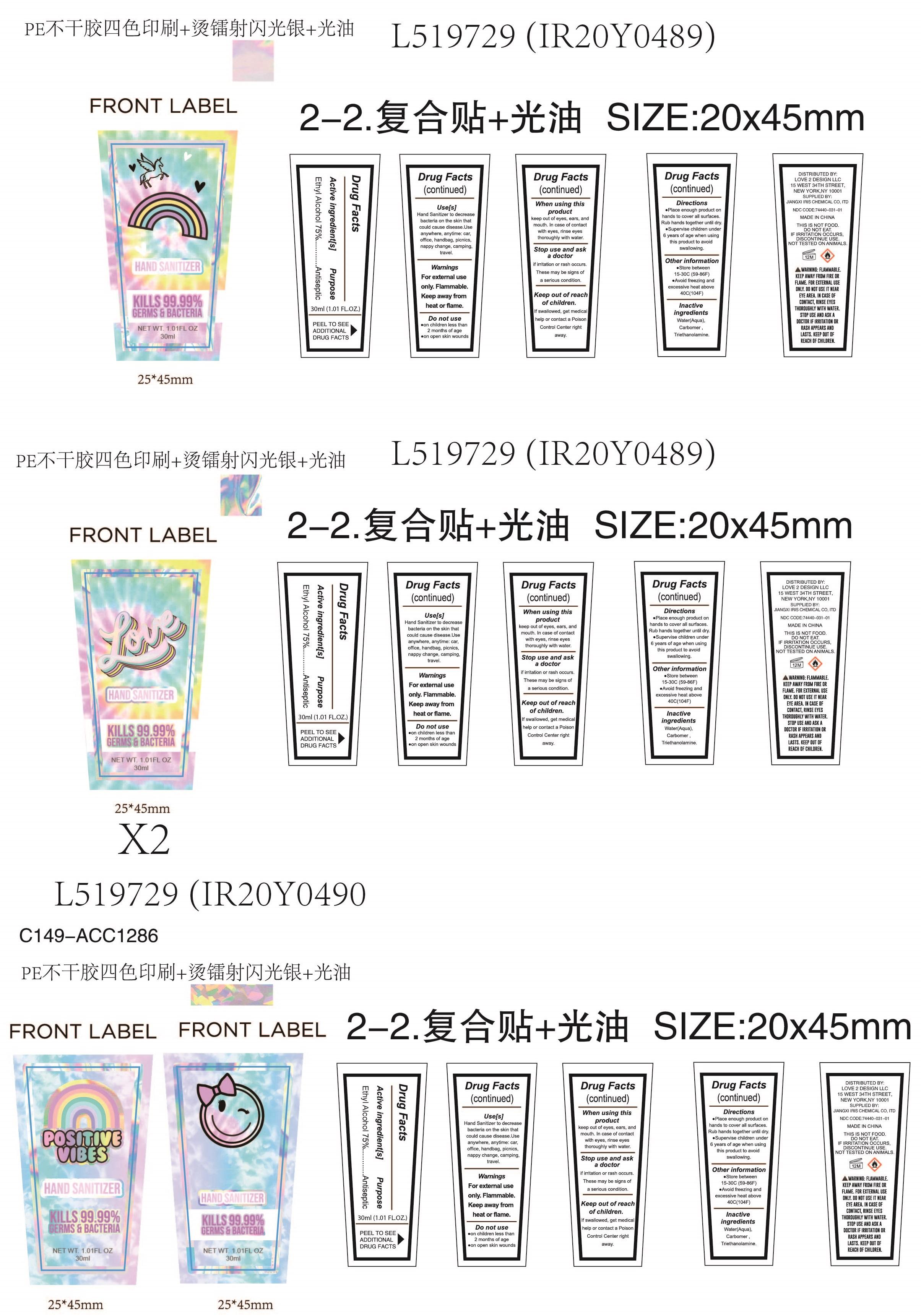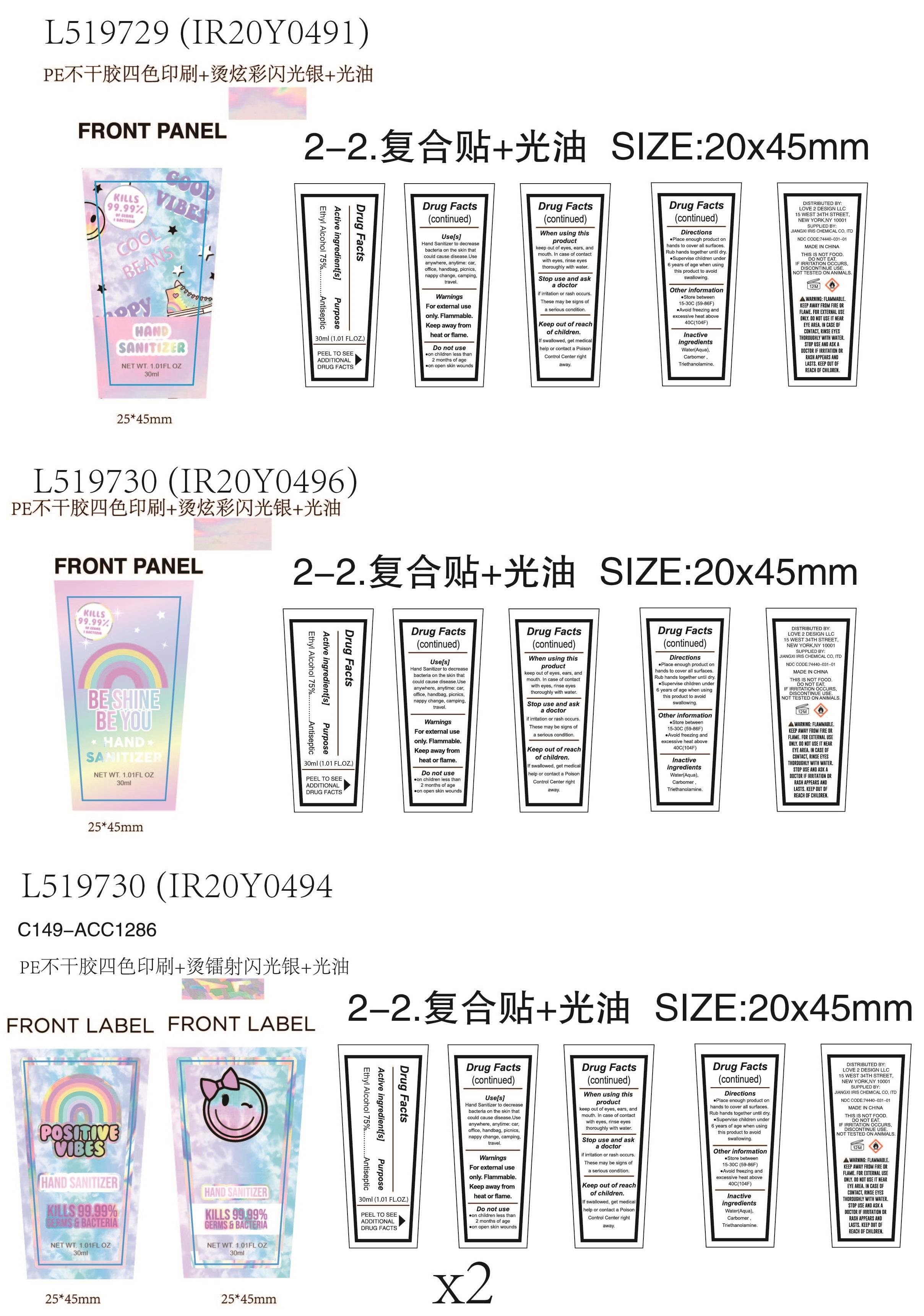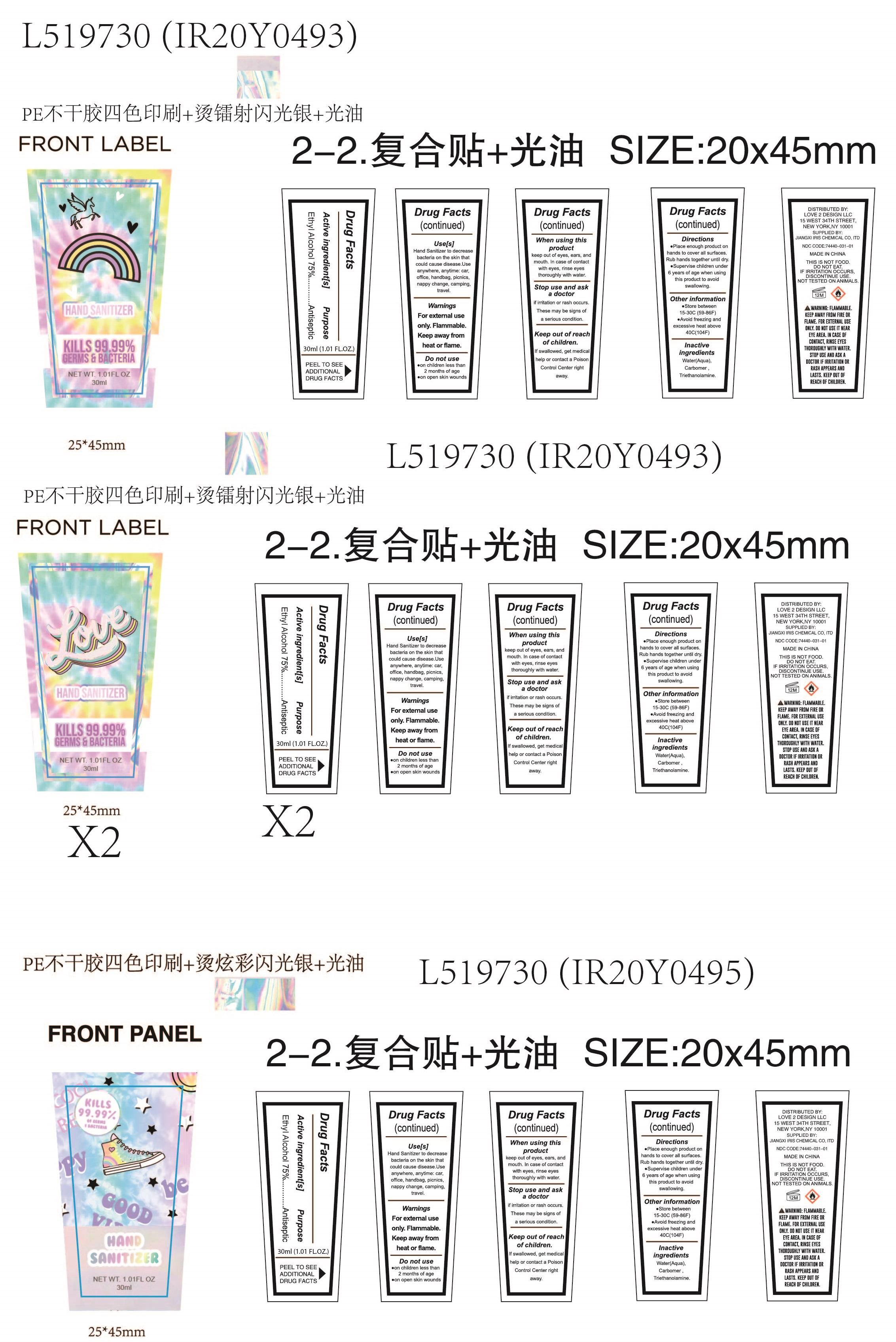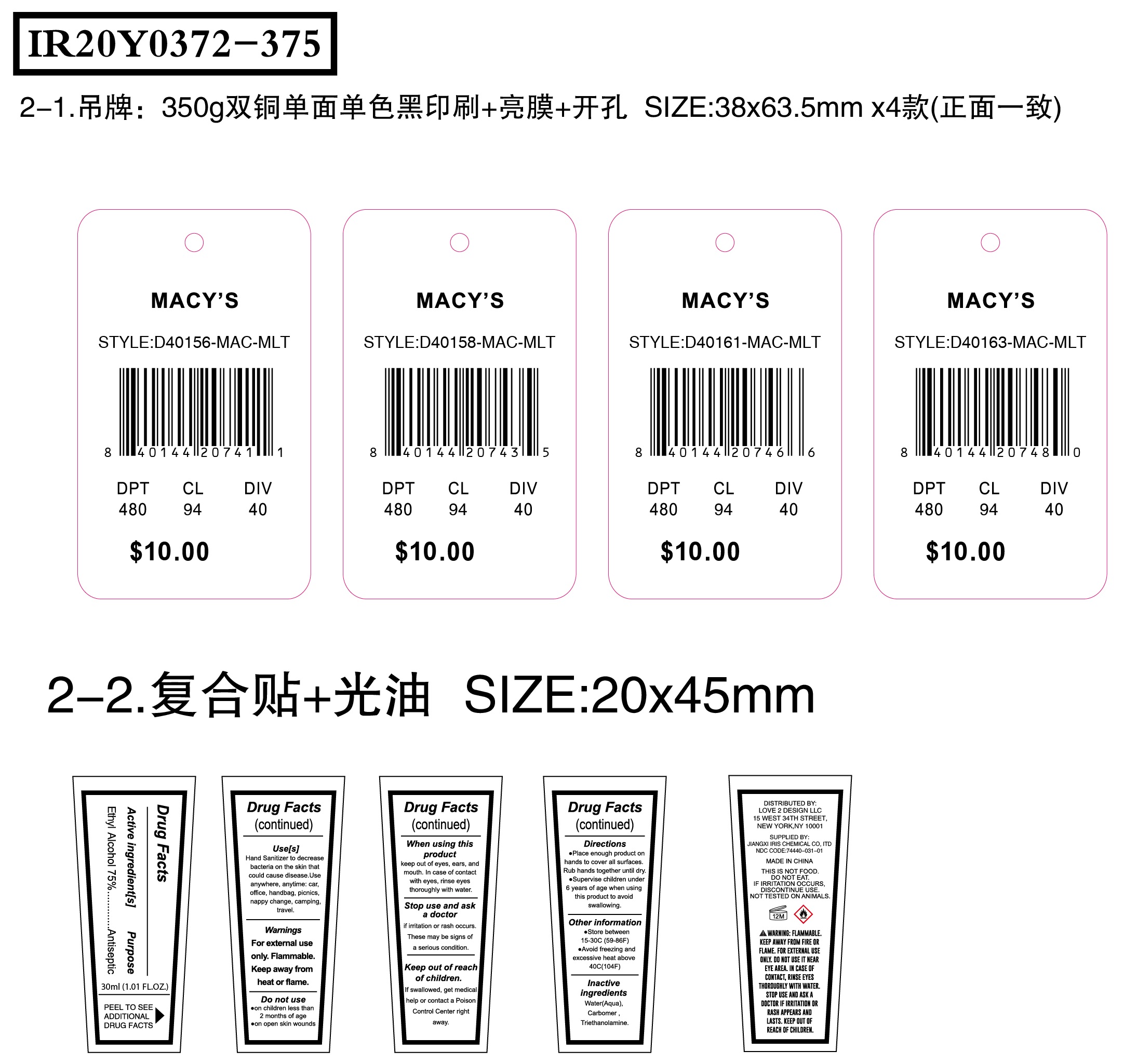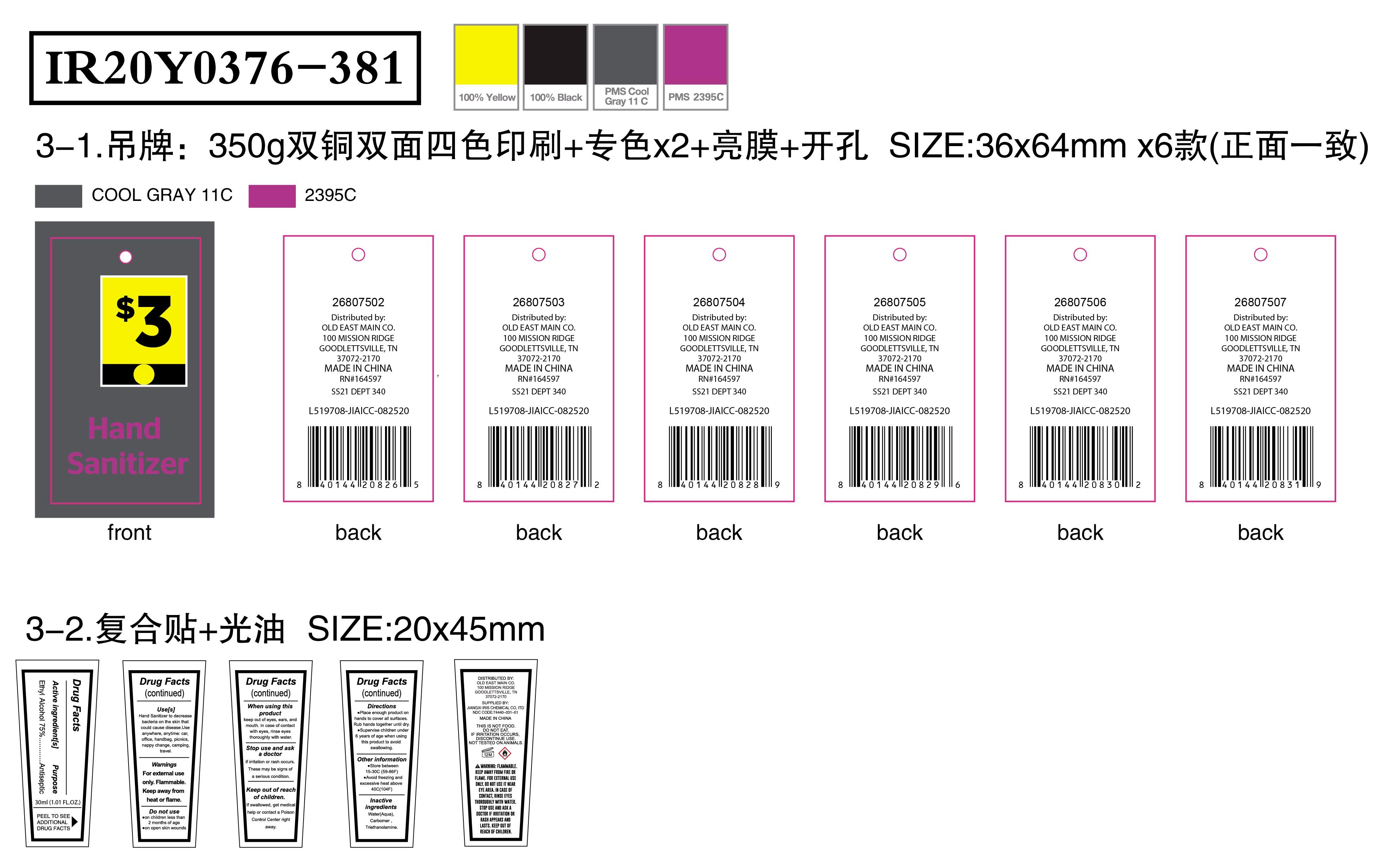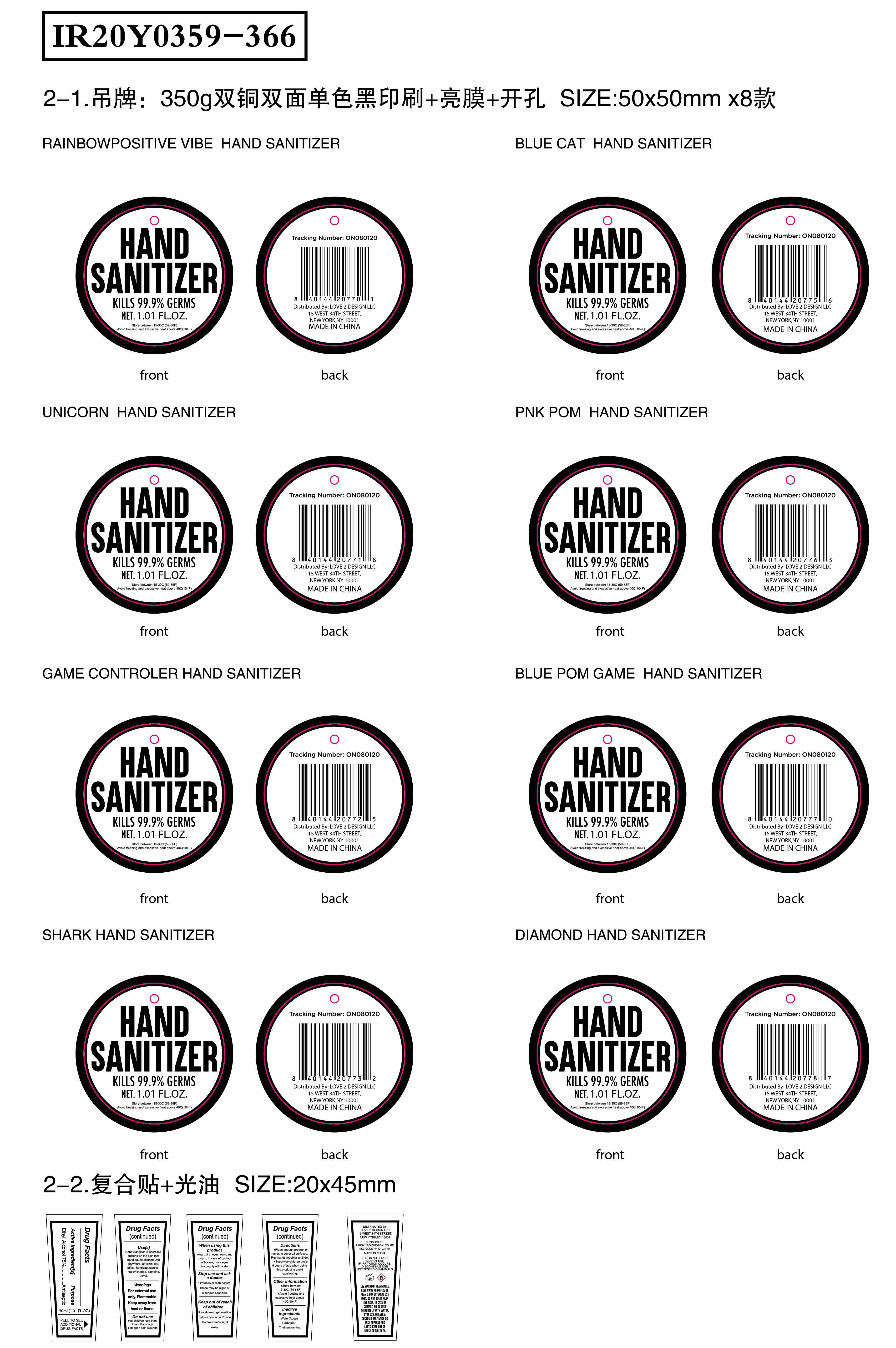 DRUG LABEL: HAND SANITIZER
NDC: 74440-031 | Form: GEL
Manufacturer: Jiangxi Iris Chemical Co.,Ltd
Category: otc | Type: HUMAN OTC DRUG LABEL
Date: 20200817

ACTIVE INGREDIENTS: ALCOHOL 75 mL/100 mL
INACTIVE INGREDIENTS: TROLAMINE; WATER; CARBOMER HOMOPOLYMER, UNSPECIFIED TYPE

031 HAND SANITIZER

Active ingredient[s]

ethyl Alcohol 75%V/v.

Purpose

Antiseptic

Use[s]

Hand sanitizer to decrease bacteria on the skin that could cause disease. Use anywhere, anytime: car,office, hand bag, picnics,nappy change, campingt ravel

Warnings

For external use only.Flammable. Keep away from fire or flame

Do not use

on children less than 2 months of age

on open skin wounds

When using this product

keep out of eyes,ears, and mouth.In case of contact with eyes,rinse eyes thoroughly with water.

Stop use and ask a doctor

if irritation or rash occurs.These may be signs of a serious condition.

keep out of reach of children. If swallowed, get medical help or contact a Poison Control Center right away.

Directions

Place enough product on hands to cover all surfaces.Rub hands together until dry.
Supervise children under 6 years of age when using this product to avoid swallowing

Other information

Store between 15-30°C(59-86°F)
Avoid freezing andexcessive heat above40°C(104°F)

Inactive ingredients

water(aqua), carbomer, triethanolamine